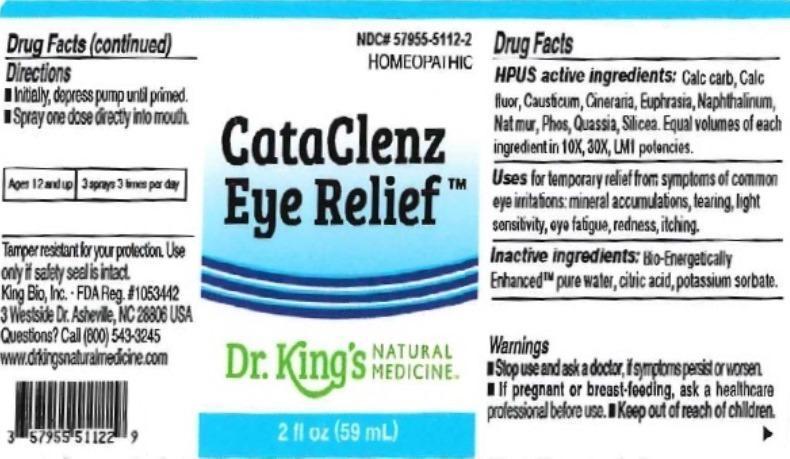 DRUG LABEL: CataClenz Eye Relief
NDC: 57955-5112 | Form: LIQUID
Manufacturer: King Bio Inc.
Category: homeopathic | Type: HUMAN OTC DRUG LABEL
Date: 20151029

ACTIVE INGREDIENTS: OYSTER SHELL CALCIUM CARBONATE, CRUDE 10 [hp_X]/59 mL; CALCIUM FLUORIDE 10 [hp_X]/59 mL; CAUSTICUM 10 [hp_X]/59 mL; JACOBAEA MARITIMA 10 [hp_X]/59 mL; EUPHRASIA STRICTA 10 [hp_X]/59 mL; NAPHTHALENE 10 [hp_X]/59 mL; SODIUM CHLORIDE 10 [hp_X]/59 mL; PHOSPHORUS 10 [hp_X]/59 mL; QUASSIA AMARA WOOD 10 [hp_X]/59 mL; SILICON DIOXIDE 10 [hp_X]/59 mL
INACTIVE INGREDIENTS: WATER; ANHYDROUS CITRIC ACID; POTASSIUM SORBATE

CataClenz Eye Relief

ACTIVE INGREDIENT

Drug Facts__________________________________________________________________________________________________________

HPUS active ingredients: Calcarea carbonica, Calcarea fluorica, Causticum, Cineraria maritima, Euphrasia officinalis, Naphthalinum, Natrum muriaticum, Phosphorus, Quassia amara, Silicea. Equal volumes of each ingredient in 10X, 30X, LM1 potencies.

INDICATIONS AND USAGE

Uses for temporary relief from symptoms of common eye irritations: mineral accumulations, tearing, light sensitivity, eye fatigue, redness, itching.

Inactive Ingredients:

Bio-Energetically Enhanced™ pure water, citric acid and potassium sorbate.

Warnings

- Stop use and ask your doctor if symptoms persist or worsen.
- If pregnant or breast-feeding, ask a healthcare professional before use.

- Keep out of reach of children.

Directions

- Initially, depress pump until primed.
- Spray one dose directly into mouth.
- Adults 12 and up: 3 sprays 3 times per day.

OTHER SAFETY INFORMATION

Tamper resistant for your protection. Use only if seal is intact.

PURPOSE

Uses for temporary relief from symptoms of common eye irritations:

- mineral accumulations
- tearing
- light sensitivity
- eye fatigue
- redness
- itching